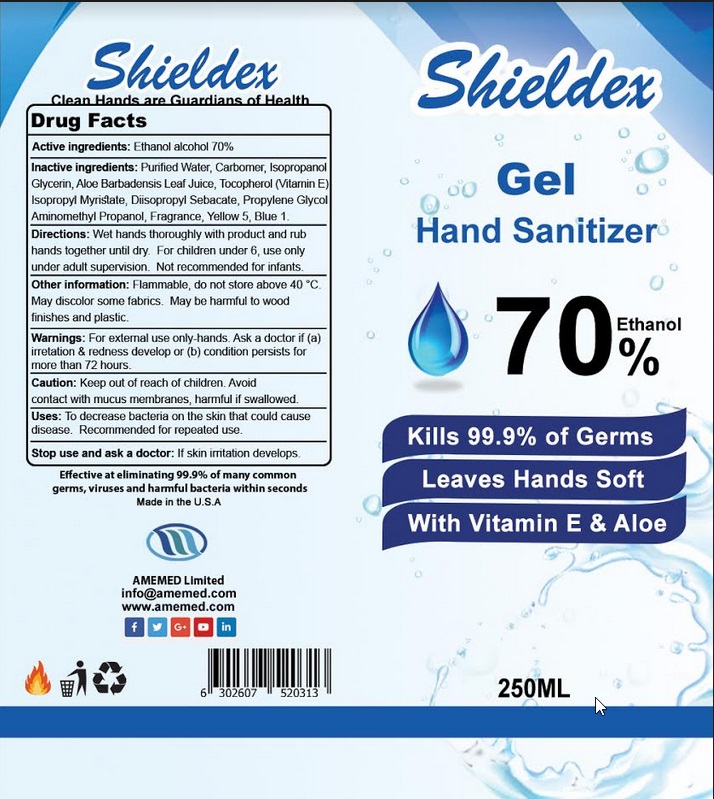 DRUG LABEL: Shield-EX hand sanitizer
NDC: 80736-002 | Form: LIQUID
Manufacturer: AMEMed
Category: otc | Type: HUMAN OTC DRUG LABEL
Date: 20201001

ACTIVE INGREDIENTS: ALCOHOL 70 mL/100 mL
INACTIVE INGREDIENTS: WATER; CARBOMER HOMOPOLYMER TYPE C; ISOPROPYL ALCOHOL; ISOPROPYL MYRISTATE; DIISOPROPYL SEBACATE; PROPYLENE GLYCOL; AMINOMETHYLPROPANOL; FRAGRANCE CLEAN ORC0600327; FD&C YELLOW NO. 5; FD&C BLUE NO. 1

Active Ingredient

Ethanol Alchohol 70%

Use

To decrease bacteria on the skin that could cause disease. Recommended for repeated use.

Warnings

For External Use Only - hands.

Ask a doctor if (a) irritation & redness develop or (b) condition persists for more than 72 hours.

Caution: Keep out of reach of children. Avoid contact with mucus membrane, harmful if swallowed.

Stop use and ask a doctor if skin irritation develops.

Directions

- Wet hands thoroughly with product and rub hands together until dry.
- For children under 6, use only under adult supervision.
- Not recommended for infants.

Other information

Flammable, do not store above 40 °C.
May discolor some fabrics. May be harmful to wood finishes and plastic.

Inactive ingredients

Purified Water, Carbomer, lsopropanol, lsopropyl Myiristate, Diisopropyl Sebacate, Propylene glycol, Aminomethyl Propanol, Fragrance Yellow 5, Blue 1.